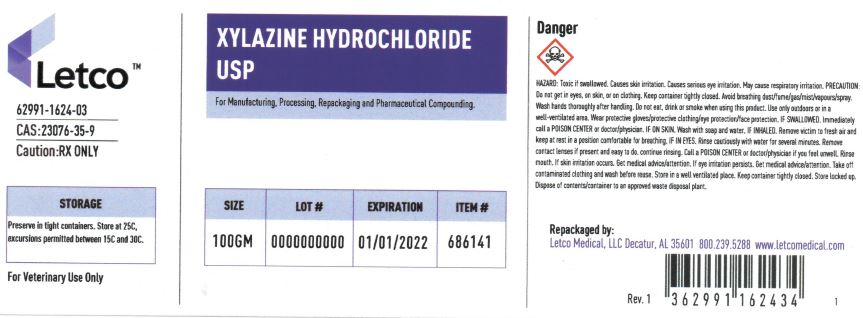 DRUG LABEL: Xylazine hydrochloride
NDC: 62991-1624 | Form: POWDER
Manufacturer: LETCO MEDICAL, LLC
Category: other | Type: BULK INGREDIENT - ANIMAL DRUG
Date: 20220418

ACTIVE INGREDIENTS: XYLAZINE HYDROCHLORIDE 1 g/1 g

Xylazine Hcl

PACKAGE LABEL

Xylazine Hydrochloride USP 100gm